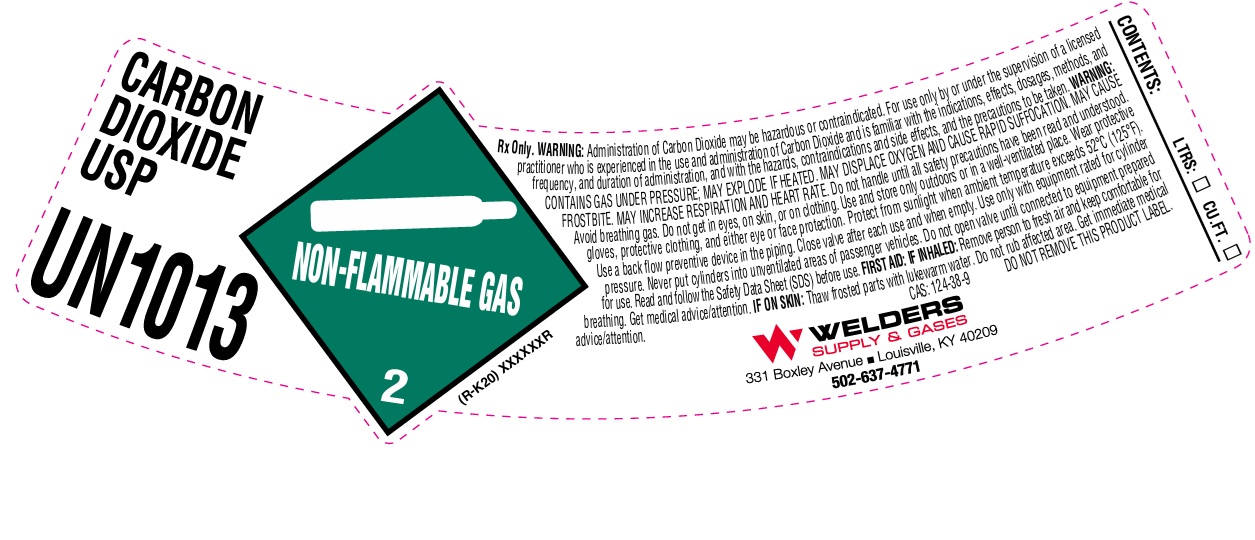 DRUG LABEL: Carbon Dioxide
NDC: 84078-003 | Form: GAS
Manufacturer: WELDERS SUPPLY COMPANY OF LOUISVILLE, INC.
Category: prescription | Type: HUMAN PRESCRIPTION DRUG LABEL
Date: 20260128

ACTIVE INGREDIENTS: CARBON DIOXIDE 990 mL/1 L

Carbon Dioxide

PACKAGE LABEL

CARBON DIOXIDE USP

UN1013

Rx Only. WARNING: Administration of Carbon Dioxide may be hazardous or contraindicated. For use only by or under the supervision of a licensed practitioner who is experienced in the use and administration of Carbon Dioxide and is familiar with the indications, effects, dosages, methods, and frequency, and duration of administration, and with the hazards, contraindications and side effects, and the precautions to be taken. WARNING: CONTAINS GAS UNDER PRESSURE; MAY EXPLODE IF HEATED. MAY DISPLACE OXYGEN AND CAUSE RAPID SUFFOCATION. MAY CAUSE FROSTBITE. MAY INCREASE RESPIRATION AND HEART RATE. Do not handle until all safety precautions have been read and understood. Avoid breathing gas. Do not get in eyes, on skin, or on clothing. Use and store only outdoors or in a well-ventilated place. Wear protective gloves, protective clothing, and either eye or face protection. Protect from sunlight when ambient temperature exceeds 52 C (125 F). Use a back flow preventive device in the piping. Close valve after each use and when empty. Use only with equipment rated for cylinder pressure. Never put cylinders into unventilated areas of passenger vehicles. Do not open valve until connected to equipment prepared for use. Read and follow the Safety Data Sheet (SDS) before use. FIRST AID: IF INHLAED: Remove person to fresh air and keep comfortable for breathing. Get medical advice/attention. IF ON SKIN: Thaw frosted parts with lukewarm water. Do not rub affected area. Get immediate medical advice/attention.

CAS: 124-38-9 DO NOT REMOVE THIS PRODUCT LABEL.

WELDERS SUPPLY & GASES

331 Boxley Avenue Louisville, KY 40209

502-637-4771

CONTENTS: LTRS: CU.FT.